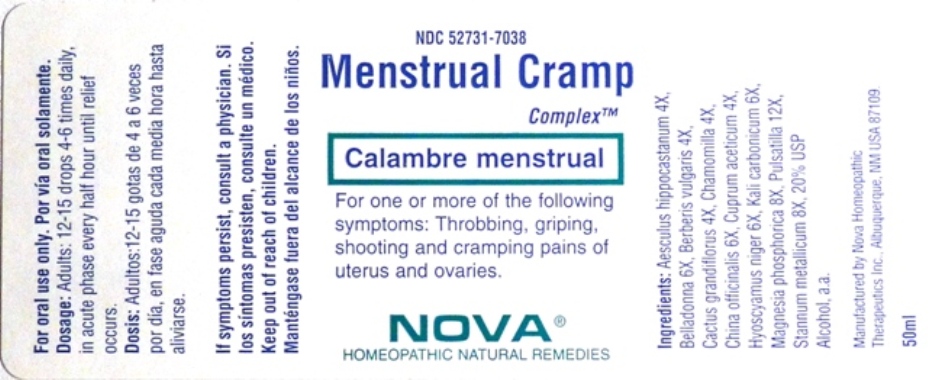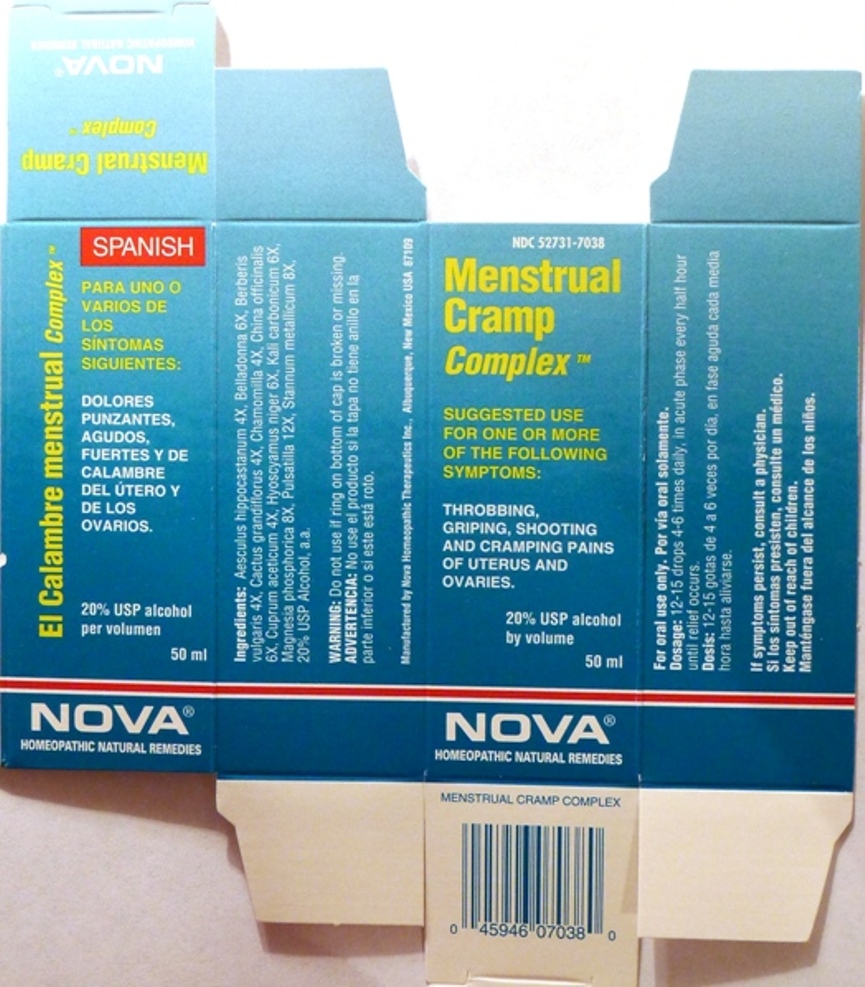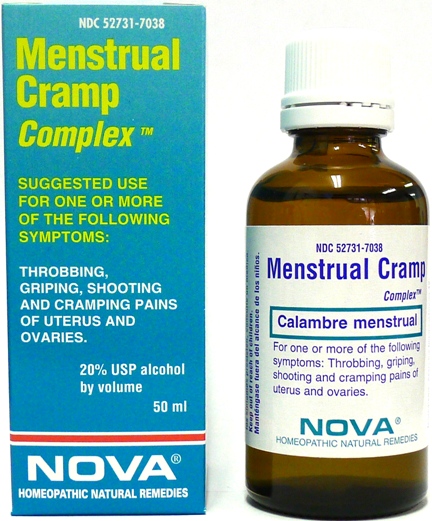 DRUG LABEL: Menstrual Cramp Complex
NDC: 52731-7038 | Form: LIQUID
Manufacturer: Nova Homeopathic Therapeutics, Inc.
Category: homeopathic | Type: HUMAN OTC DRUG LABEL
Date: 20110601

ACTIVE INGREDIENTS: HORSE CHESTNUT 4 [hp_X]/1 mL; ATROPA BELLADONNA 6 [hp_X]/1 mL; BERBERIS VULGARIS ROOT BARK 4 [hp_X]/1 mL; SELENICEREUS GRANDIFLORUS STEM 4 [hp_X]/1 mL; MATRICARIA RECUTITA 4 [hp_X]/1 mL; CINCHONA PUBESCENS BARK 6 [hp_X]/1 mL; CUPRIC ACETATE 4 [hp_X]/1 mL; HYOSCYAMUS NIGER 6 [hp_X]/1 mL; POTASSIUM CARBONATE 6 [iU]/1 mL; MAGNESIUM PHOSPHATE, DIBASIC TRIHYDRATE 8 [hp_X]/1 mL; PULSATILLA VULGARIS 12 [hp_X]/1 mL; TIN 8 [hp_X]/1 mL
INACTIVE INGREDIENTS: ALCOHOL

Menstrual Cramp Complex

Purpose:

Suggested use for one or more of the following symptoms:

Throbbing, gripping, shooting and cramping pains of uterus and ovaries.

Usage and Dosage:

For oral use only.

DOSAGE AND ADMINISTRATION

Adults:
In Acute Phase:
12-15 drops, every half hour until relief occurs
When Relief Occurs:
12-15 drops, 4-6 times per day

Warnings:

Keep out of reach of children.

WARNINGS

If symptoms persist, consult a physician.
Do not use if ring on bottom of cap is broken or missing.

Active Ingredients:

Aesculus hippocastanum 4X, Belladonna 6X, Berberis vulgaris 4X, Cactus grandiflorus 4X, Chamomilla 4X, China officinalis 6X, Cuprum aceticum 4X, Hyoscyamus niger 6X, Kali carbonicum 6X, Magnesia phosphorica 8X, Pulsatilla 12X, Stannum metallicum 8X

Inactive Ingredients:

Alcohol, 20% USP

QUESTIONS

Manufactured by Nova Homeopathic Therapeutics Inc., Albuquerque, New Mexico USA 87109
1-800-225-8094

PACKAGE LABEL

Menstrual Cramp Complex Product

Menstrual Cramp Complex Bottle Label

Menstrual Cramp Complex Box